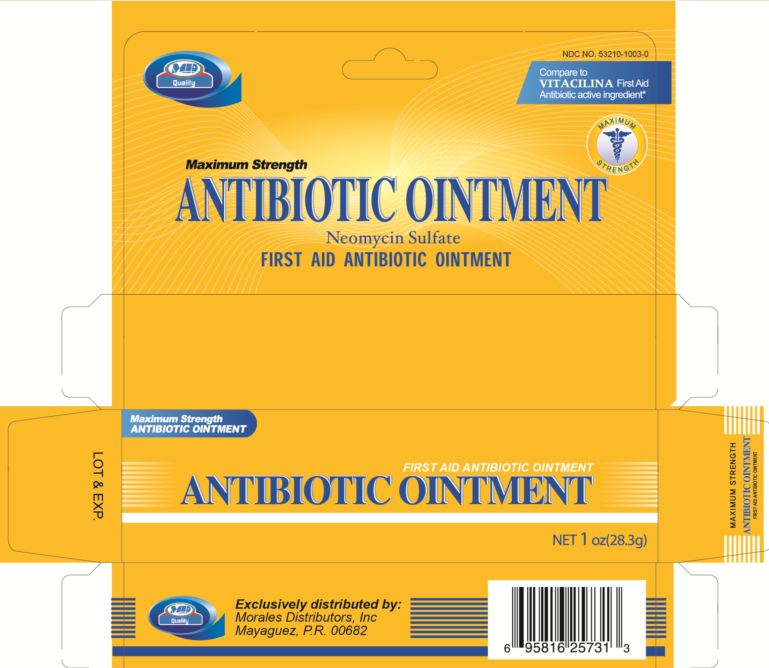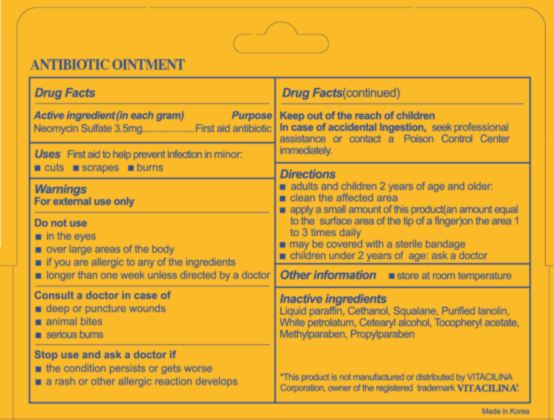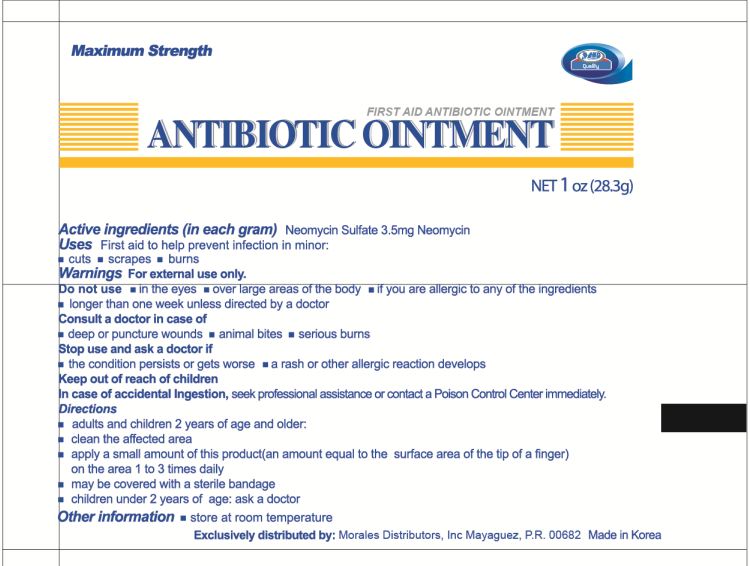 DRUG LABEL: Antibiotic
                
                
NDC: 53210-1003 | Form: OINTMENT
Manufacturer: Morales Distributors Inc
Category: otc | Type: HUMAN OTC DRUG LABEL
Date: 20120928

ACTIVE INGREDIENTS: NEOMYCIN SULFATE 3.5 mg/1 g
INACTIVE INGREDIENTS: MINERAL OIL; SQUALANE; LANOLIN; PETROLATUM; CETOSTEARYL ALCOHOL; .ALPHA.-TOCOPHEROL ACETATE; METHYLPARABEN; PROPYLPARABEN

Antibiotic Ointment

Active ingredients (in each gram)

Neomycin Sulfate 3.5mg

Purpose

First aid antibiotic

Uses

First aid to help prevent infection in minor:

- cuts
- scrapes
- burns

Warnings

For external use only

Do not use

- in the eyes
- over large areas of the body
- if you are allergic to any of the ingredients
- longer than one week unless directed by a doctor

Consult a doctor in case of

- deep or puncture wounds
- animal bites
- serious burns

Stop use and ask a doctor if

- the condition persists or gets worse
- a rash or other allergic reaction develops

Keep out of reach of children

in case of accidental ingestion, seek professional assistance or contact a Poison Control Center immediately.

Directions

- adults and children 2 years of age and older
- clean the affected area
- apply a small amount of this product(an amount equal to the surface area of the tip of a finger) on the area 1 to 3 times daily
- may be covered with a sterile bandage
- children under 2 years of age: ask a doctor

Other information

store at room temperature

Inactive ingredients

Liquid paraffin, Cethanol, Squalane, Purified lanolin, White petrolatum, Cetearyl alcohol, Tocopheryl acetate, Methylparaben, Propylparaben

Package label

NDC NO. 53210-1003-0
Compare to Vitacilinia First Aid Antibiotic active ingredient

MAXIMUM STRENGTH

ANTIBIOTIC OINTMENT
Neomycin Sulfate
FIRST AID ANTIBIOTIC OINTMENT

Net 1 oz (28.3g)

Exclusively distributed by:
Morales Distributors, Inc.
Mayaguez, P.R. 00682

Made in Korea